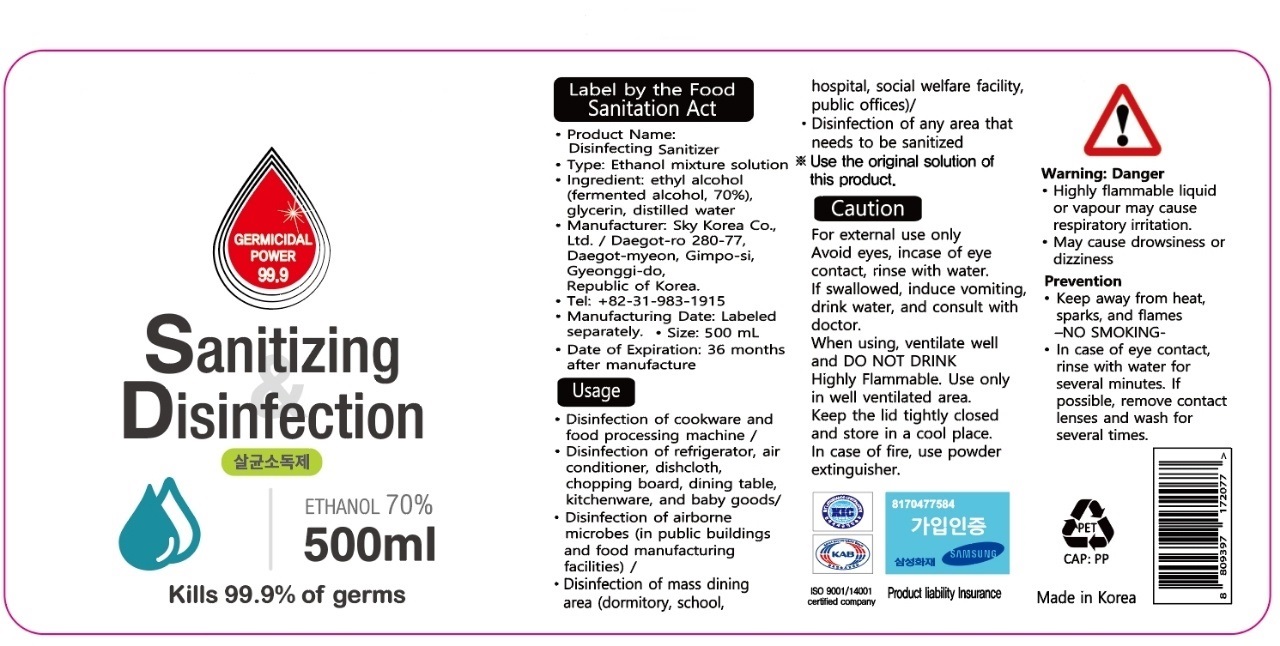 DRUG LABEL: Sanitizing Disinfection
NDC: 76863-0002 | Form: LIQUID
Manufacturer: Sky korea Co Ltd
Category: otc | Type: HUMAN OTC DRUG LABEL
Date: 20200925

ACTIVE INGREDIENTS: ALCOHOL 70 mL/100 mL
INACTIVE INGREDIENTS: GLYCERIN; WATER

Drug Facts

ACTIVE INGREDIENT

alcohol

INACTIVE INGREDIENT

glycerol

PURPOSE

Sterilization of hands and skin

KEEP OUT OF REACH OF THE CHILDREN

INDICATIONS AND USAGE

apply Where sterilization is required.

WARNINGS

■ Flammable. Keep away from fire or flame.

■ For external use only.

■ Do not use in eyes.

■ lf swallowed, get medical help promptly.

■ Stop use, ask doctor lf irritation occurs.

■ Keep out of reach of children.

DOSAGE AND ADMINISTRATION

for external use only